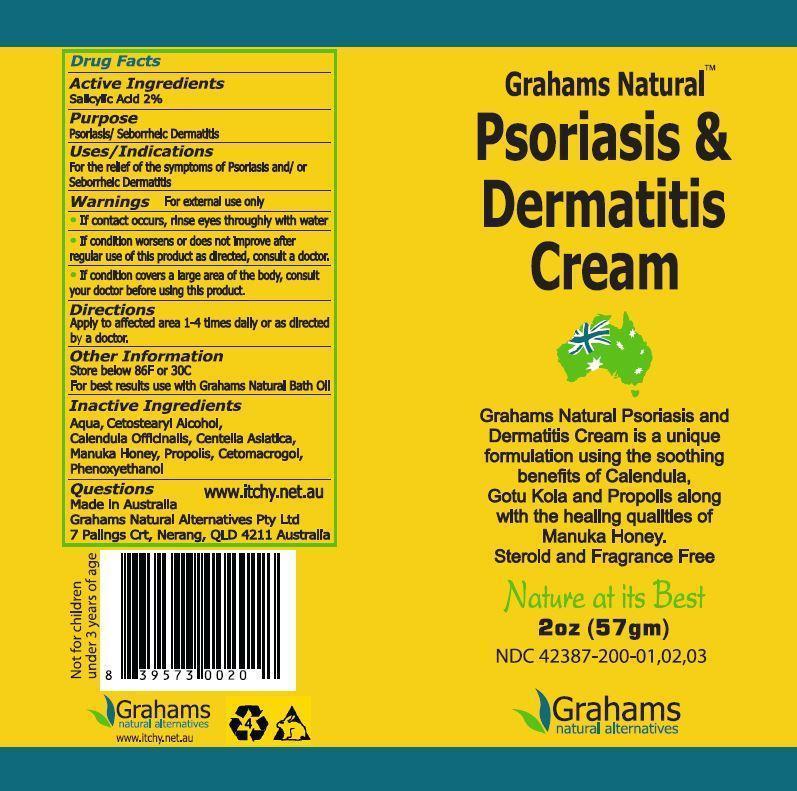 DRUG LABEL: Grahams Natural Psoriasis and Dermatitis
NDC: 42387-200 | Form: CREAM
Manufacturer: Grahams Natural Alternatives Pty Ltd
Category: otc | Type: HUMAN OTC DRUG LABEL
Date: 20150903

ACTIVE INGREDIENTS: SALICYLIC ACID 2 g/100 g
INACTIVE INGREDIENTS: WATER; CETOSTEARYL ALCOHOL; CALENDULA OFFICINALIS FLOWER; CENTELLA ASIATICA; HONEY; PROPOLIS WAX; CETETH-20; PHENOXYETHANOL

Purpose

Psoriasis/Seborrheic Dermatitis

Active Ingredients

Salicylic Acid 2%

Keep out of reach of children

Uses/Indications

For the relief of the symptoms of psoriasis and/or seborrheic dermatitis

Directions

Apply to affected area 1-4 times daily or as directed by a doctor

Warnings for external use only

If contact occurs, rinse eyes thoroughly with water

If condition worsens or does not improve after regular use of this product as directed, consult a doctor.

If condition covers a large area of the body, consult your doctor before using this product.

DESCRIPTION

Grahams Natural Psoriasis & Dermatitis Cream

Grahams Natural Psoriasis and Dermatitis Cream is a unique formulation using the soothing benefits of calendula, gotu kola and propolis along with the healing qualities of manuka honey.

steroid and fragrance free

Nature at its Best

Other Information

Store below 86F or 30C

For best results use with Grahams Natural Bath Oil

Questions www.itchy.net.au

Made in Australia

Grahams Natural Alternatives Pty Ltd

7 Palings Crt, Nerang, QLD 4211 Australia

Inactive Ingredients

aqua, cetostearyl alcohol, calendula officinalis, centella asiatica, manuka honey, propolis, cetomacrogol, phenoxyethanol